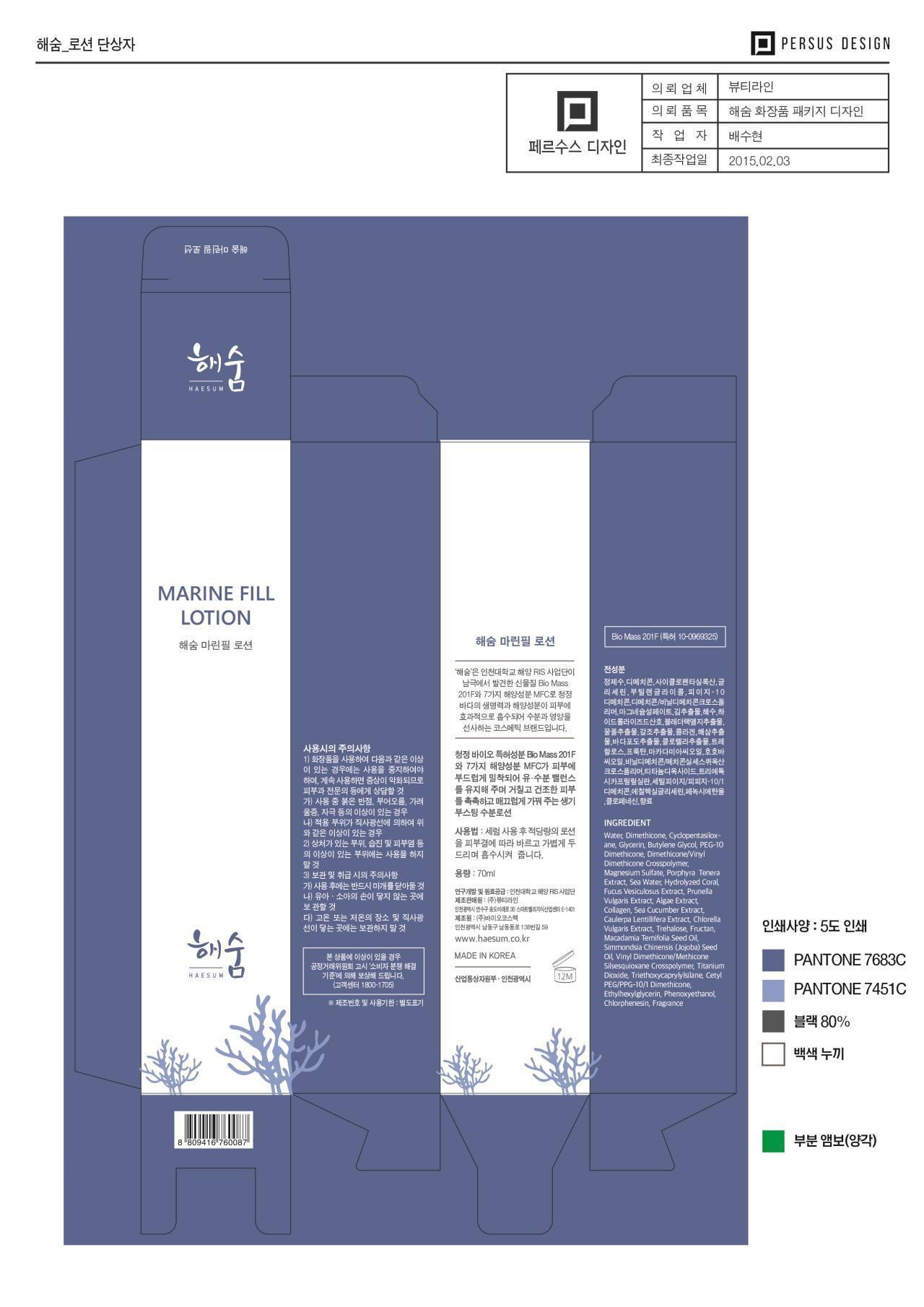 DRUG LABEL: Haesum Marine Fill
NDC: 69327-1101 | Form: LOTION
Manufacturer: Beauty Line Co., Ltd.
Category: otc | Type: HUMAN OTC DRUG LABEL
Date: 20150418

ACTIVE INGREDIENTS: GLYCERIN 3 g/100 mL
INACTIVE INGREDIENTS: WATER; BUTYLENE GLYCOL; DIMETHICONE

Drug Facts

ACTIVE INGREDIENT

glycerin

INACTIVE INGREDIENT

water, butylene glycol, sea water, dimethicone, algae ext, collagen, etc.

PURPOSE

skin protectant

keep out or reach of the children

INDICATIONS AND USAGE

apply proper amount to the skin

WARNINGS

-If in contact with the eyes, wash out thoroughty with water If the symptoms are servere, seek medical advice immediately
-This product is for exeternal use only. Do not use for internal use
-If possible, avoid direct sunlight and store in cool and area of low humidity
-In order to maintain the quality of the product and avoid misuse
-Avoid placing the product near fire and store out in reach of children

DOSAGE AND ADMINISTRATION

for external use only